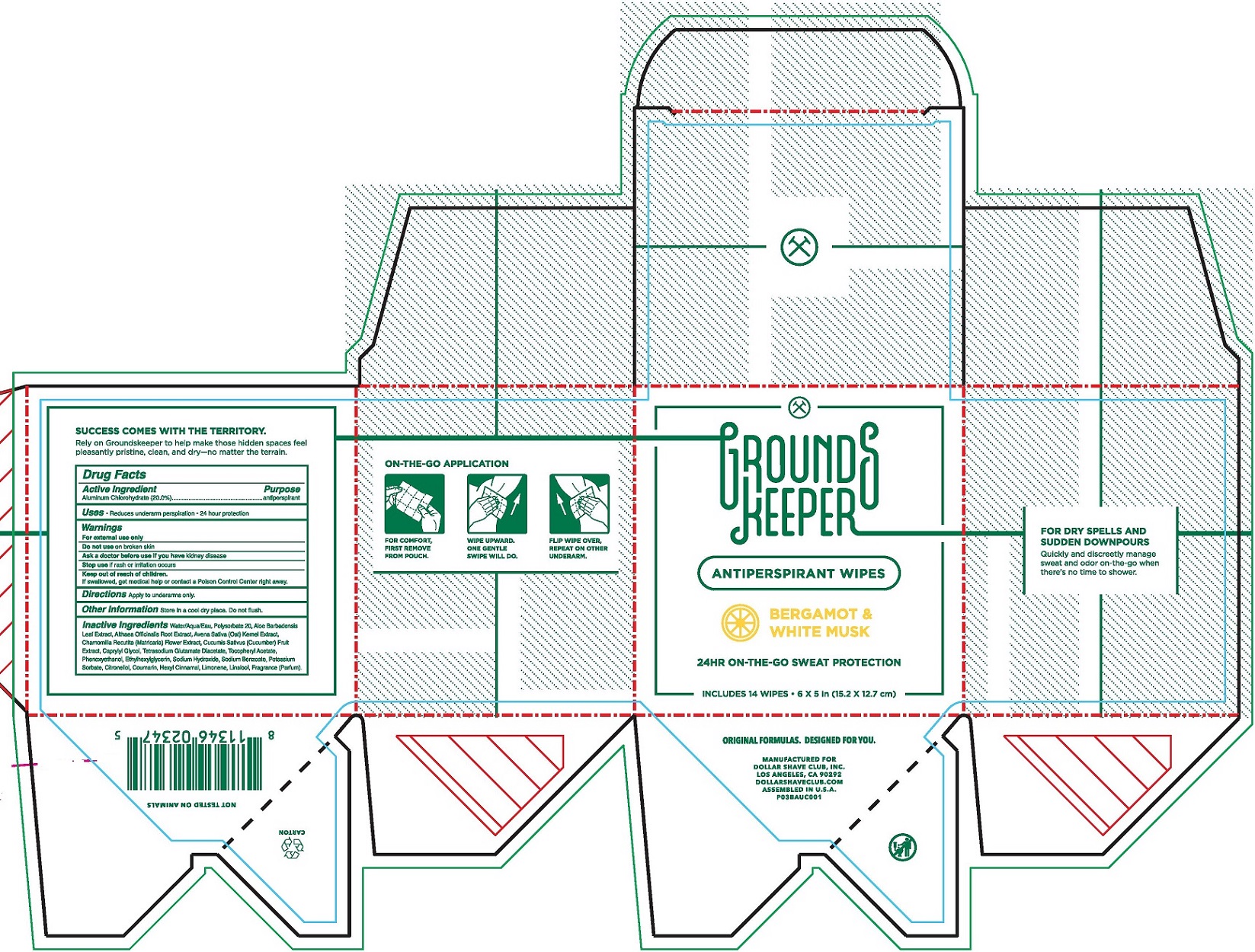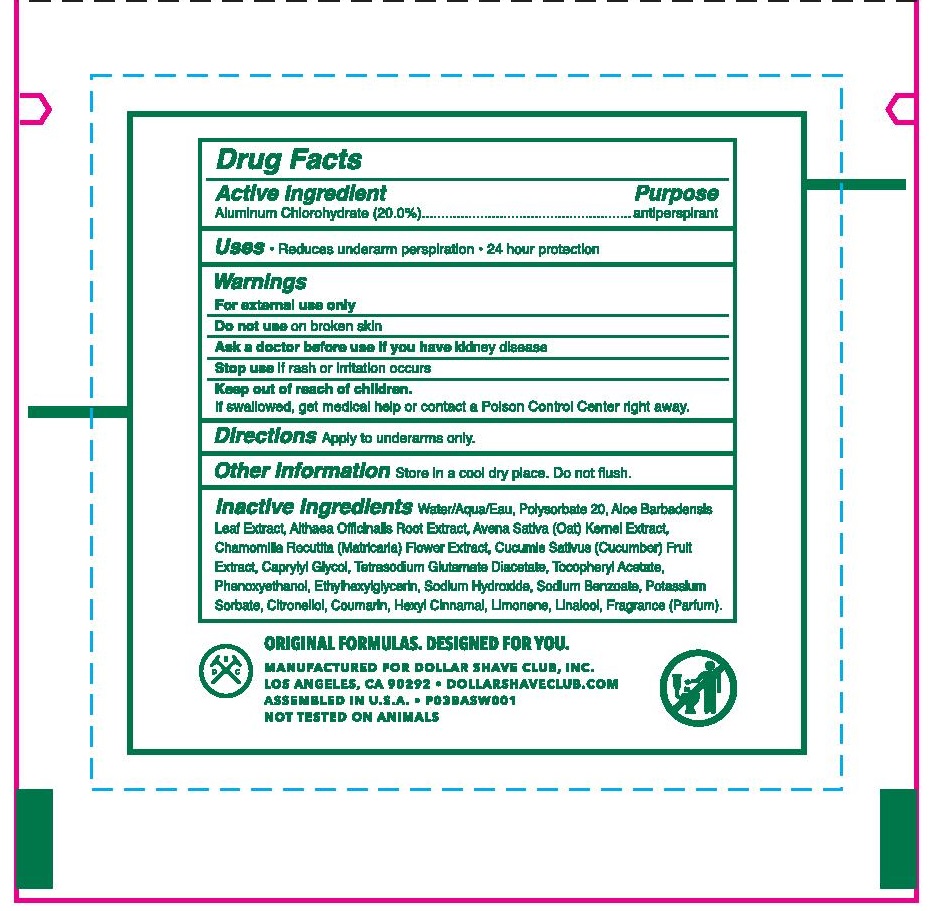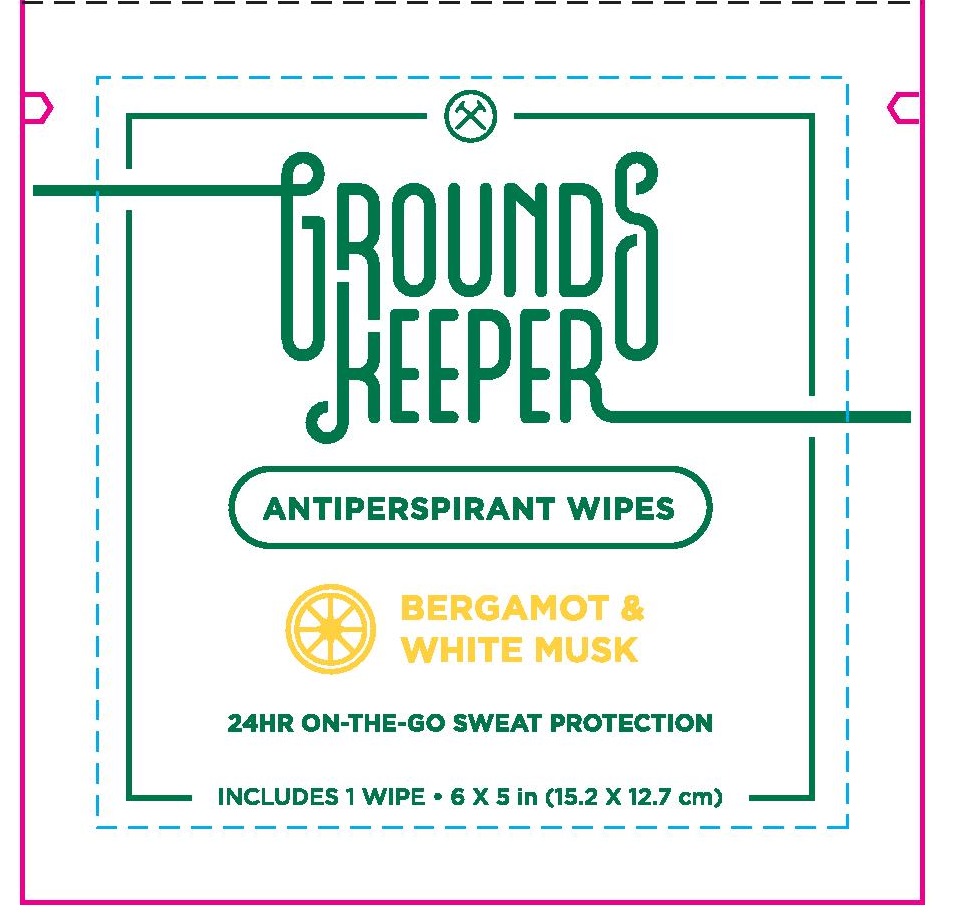 DRUG LABEL: Grounds Keeper Antiperspirant Wipes Bergamot and White Musk
NDC: 69522-2617 | Form: CLOTH
Manufacturer: Dollar Shave Club
Category: otc | Type: HUMAN OTC DRUG LABEL
Date: 20190801

ACTIVE INGREDIENTS: ALUMINUM CHLOROHYDRATE 0.2 mg/1 mL
INACTIVE INGREDIENTS: LONICERA JAPONICA FLOWER; LACTIC ACID, L-; LONICERA CAPRIFOLIUM FLOWER; WATER; ALOE VERA LEAF; GLUCONIC ACID; SODIUM BENZOATE

Active Ingredient

Aluminum Chlorohydrate (20.0%)

Purpose

Antiperspirant

Uses

- Reduces underarm perspiration
- 24 hour protection

Warnings

- For external use only
- Do not use on broken skin
- Ask a doctor before use if you have Kidney disease
- Stop use if rash or irritation occurs

Keep out of reach of children

If swallowed, get medical help or contact a Poison Control Center right away

Directions

Apply to underarms only.

Other Inforamtion

Store in a cool dry place. Do not flush.

Inactive Ingredients

Water/Aqua/Eau,Polysorbate 20, Aloe Barbadensis, Leaf Extract, Althaea Officinalis Root Extract, Avena Sativa (Oat) Kernel Extract,Chamomilla Recutita (Matricaria) Flower Extract, Cucumis Sativus (Cucumber) Fruit Extract, Caprylyl Glycol,Tetrasodium Glutamate Diacetate, Tocopheryl Acetate, Phenoxyethanol, Ethylhexylglycerin, Sodium Hydroxide, Sodium Benzoate, Potassium Sorbate, Alpha-Isomethyl Ionone, Benzyl Salicylate, Citral, Citronellol, Geraniol, Limonene, Linalool, Fragrance (parfum)

Label

GROUNDSKEEPER

ANTIPERSPIRANT WIPES

BERGAMONT AND WHITE MUSK

24HR ON-THE-GO SWEAT PROTECTION

INCLUDES 14 WIPES 6X5 IN (15.2 X 12.7 CM)

ORIGINAL FORMULAS. DESIGNED FOR YOU.

MANUFACTURED FOR DOLLAR SHAVE CLUB

LOS ANAGELES, CA 90292

DOLLAR SHAVE CLUB.COM

ASSEMBLED IN U.S.A.

PO35AUC001

FOR DRY SPELLS AND SUDEN DOWNPOURS

QUICKLY AND DISCREETLY MANAGE SWEAT AND ODOR ON-THE-GO WHEN THERE'S NO TIME TO SHOWER

ON-THE-GO APPLICATION

FOR COMFORT, FIRST REMOVE FROM POUCH, WIPE UPWARD. ONE GENTLE SWIPE WILL DO. FLIP WIPE OVER, REPEAT ON OTHER UNDERARM

SUCCESS COMES WITH THE TERRITORY

Rely on Groundskeeper to help make those hidden spaces feel pleasantly pristine, clean and dry - no matter the terrain.

NOT TESTED ON ANIMALS